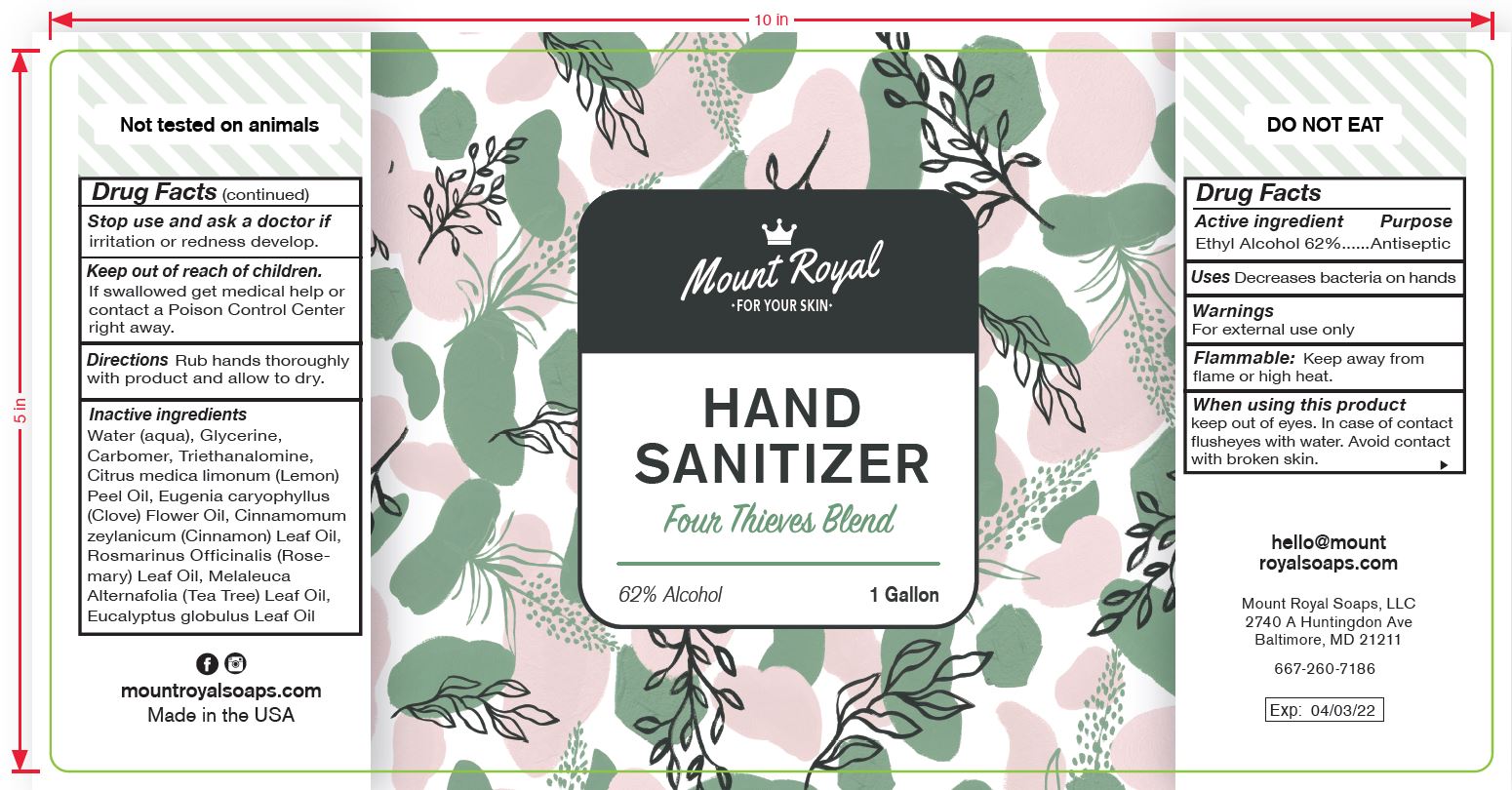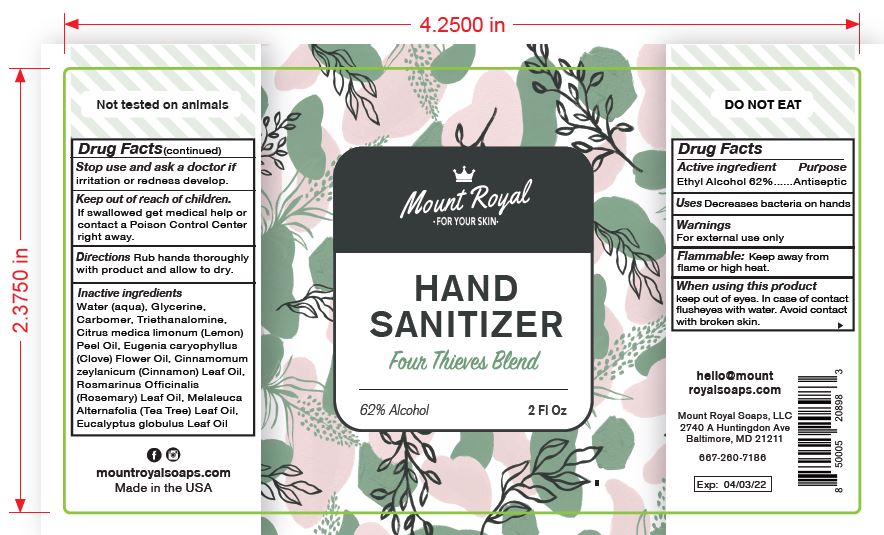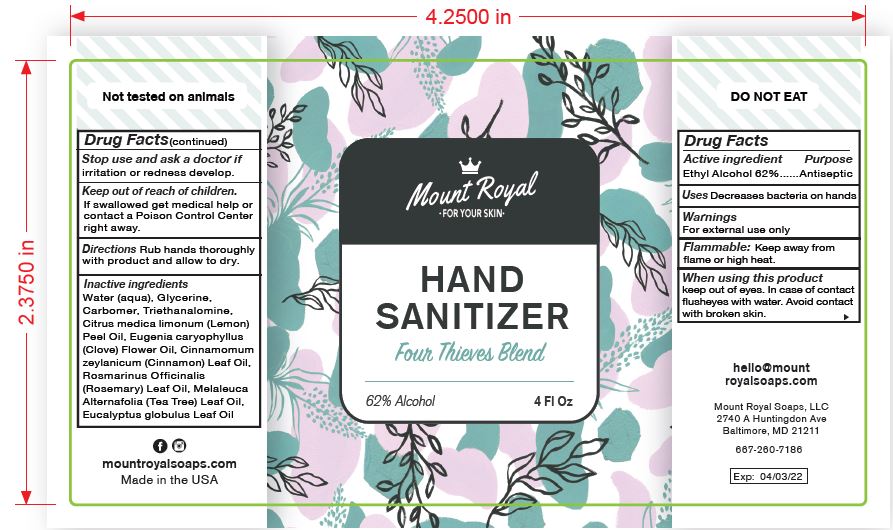 DRUG LABEL: Hand Sanitizer - Four Thieves Blend
NDC: 74322-002 | Form: GEL
Manufacturer: Mount Royal Soaps, LLC
Category: otc | Type: HUMAN OTC DRUG LABEL
Date: 20200403

ACTIVE INGREDIENTS: ALCOHOL 63 mL/100 mL
INACTIVE INGREDIENTS: LEMON OIL 0.19 mL/100 mL; ROSEMARY OIL 0.13 mL/100 mL; TEA TREE OIL 0.13 mL/100 mL; TROLAMINE 0.4 mL/100 mL; CLOVE OIL 0.08 mL/100 mL; EUCALYPTUS OIL 0.11 mL/100 mL; GLYCERIN 1.45 mL/100 mL; CARBOMER HOMOPOLYMER, UNSPECIFIED TYPE 0.4 mL/100 mL; WATER 34 mL/100 mL; CINNAMON LEAF OIL 0.06 mL/100 mL

Hand Sanitizer - Four Thieves Gel Blend

Product Decription & Introduction

This is a gel-form hand sanitizer (topical antiseptic rub) with a minimum of 62% Ethanol concentration and additional cosmetic fragrances manufactured in accordance with 21CFR330 and 21CFR333a.

Active Ingredient(s)

Ethyl Alcohol 62% v/v. Purpose: Antiseptic

Purpose

Antiseptic, Hand Sanitizer

Use

Decreases bacteria on hands

Warnings

For external use only

Flammable

Keep away from flame or high heat

When using this product keep out of eyes. In case of contact with eyes, flush eyes with water. Avoid contact with broken skin.

Stop use and ask a doctor if irritation or redness develop.

Keep out of reach of children. If swallowed, get medical help or contact a Poison Control Center right away.

Directions

Rub hands thoroughly with product and allow to dry.

Inactive ingredients

Water (aqua), Glycerine, Carbomer, Triethanolamine, Citrus Medica Limonum (Lemon) Peel Oil, Eugenia Caryophyllus (Clove) Flower Oil, Cinnamomum Zeylanicum (Cinnamon) Leaf Oil, Rosmarinus Officinalis (Rosemary) Leaf Oil, Melaleuca Alternifolia (Tea Tree) Leaf Oil, Eucalyptus Globulus Leaf Oil

Initial Registration

Updated label content sections from default content included in the COVID-19 Hand Sanitizer template to be consistent with product label.

Package Label - Principal Display Panel

Size: 59.1471 mL (2 Oz)

NDC: 74322-002-01

Label:

Size: 118.294 mL (4 Oz)

NDC: 74322-002-02

Label:

Size: 3785.41 mL (1 gal)

NDC: 74322-002-03

Label: